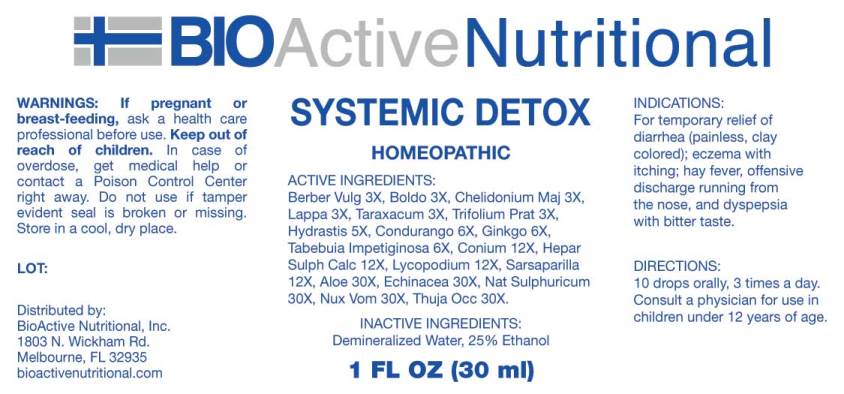 DRUG LABEL: Systemic Detox
NDC: 43857-0435 | Form: LIQUID
Manufacturer: BioActive Nutritional, Inc.
Category: homeopathic | Type: HUMAN OTC DRUG LABEL
Date: 20241018

ACTIVE INGREDIENTS: BERBERIS VULGARIS ROOT BARK 3 [hp_X]/1 mL; PEUMUS BOLDUS LEAF 3 [hp_X]/1 mL; CHELIDONIUM MAJUS WHOLE 3 [hp_X]/1 mL; ARCTIUM LAPPA ROOT 3 [hp_X]/1 mL; TARAXACUM OFFICINALE 3 [hp_X]/1 mL; TRIFOLIUM PRATENSE FLOWER 3 [hp_X]/1 mL; GOLDENSEAL 5 [hp_X]/1 mL; MARSDENIA CONDURANGO BARK 6 [hp_X]/1 mL; GINKGO 6 [hp_X]/1 mL; TABEBUIA IMPETIGINOSA BARK 6 [hp_X]/1 mL; CONIUM MACULATUM FLOWERING TOP 12 [hp_X]/1 mL; CALCIUM SULFIDE 12 [hp_X]/1 mL; LYCOPODIUM CLAVATUM SPORE 12 [hp_X]/1 mL; SMILAX ORNATA ROOT 12 [hp_X]/1 mL; ALOE 30 [hp_X]/1 mL; ECHINACEA ANGUSTIFOLIA WHOLE 30 [hp_X]/1 mL; SODIUM SULFATE 30 [hp_X]/1 mL; STRYCHNOS NUX-VOMICA SEED 30 [hp_X]/1 mL; THUJA OCCIDENTALIS LEAFY TWIG 30 [hp_X]/1 mL
INACTIVE INGREDIENTS: WATER; ALCOHOL

DRUG FACTS:

ACTIVE INGREDIENTS:

Berberis Vulgaris 3X, Boldo 3X, Chelidonium Majus 3X, Lappa Major 3X, Taraxacum Officinale 3X, Trifolium Pratense 3X, Hydrastis Canadensis 5X, Condurango 6X, Ginkgo Biloba 6X, Tabebuia Impetiginosa 6X, Conium Maculatum 12X, Hepar Sulphuris Calcareum 12X, Lycopodium Clavatum 12X, Sarsaparilla (Smilax Regelii) 12X, Aloe 30X, Echinacea (Angustifolia) 30X, Natrum Sulphuricum 30X, Nux Vomica 30X, Thuja Occidentalis 30X.

INDICATIONS:

For temporary relief of diarrhea (painless, clay colored); eczema with itching; hay fever, offensive discharge running from the nose, and dyspepsia with bitter taste.

WARNINGS:

If pregnant or breast-feeding, ask a health care professional before use.

Keep out of reach of children. In case of overdose, get medical help or contact a Poison Control Center right away.

Do not use if tamper evident seal is broken or missing.

Store in cool, dry place.

Keep out of reach of children. In case of overdose, get medical help or contact a Poison Control Center right away.

DIRECTIONS:

10 drops orally, 3 times a day. Consult a physician for use in children under 12 years of age.

INDICATIONS:

For temporary relief of diarrhea (painless, clay colored); eczema with itching; hay fever, offensive discharge running from the nose, and dyspepsia with bitter taste.

INACTIVE INGREDIENTS:

Demineralized Water, 25% Ethanol

QUESTIONS:

Distributed by:

BioActive Nutritional, Inc.

1803 N. Wickham Rd.

Melbourne, FL 32935

bioactivenutritional.com

PACKAGE LABEL DISPLAY:

BIOActive Nutritional

SYSTEMIC DETOX

HOMEOPATHIC

1 FL OZ (30 ml)